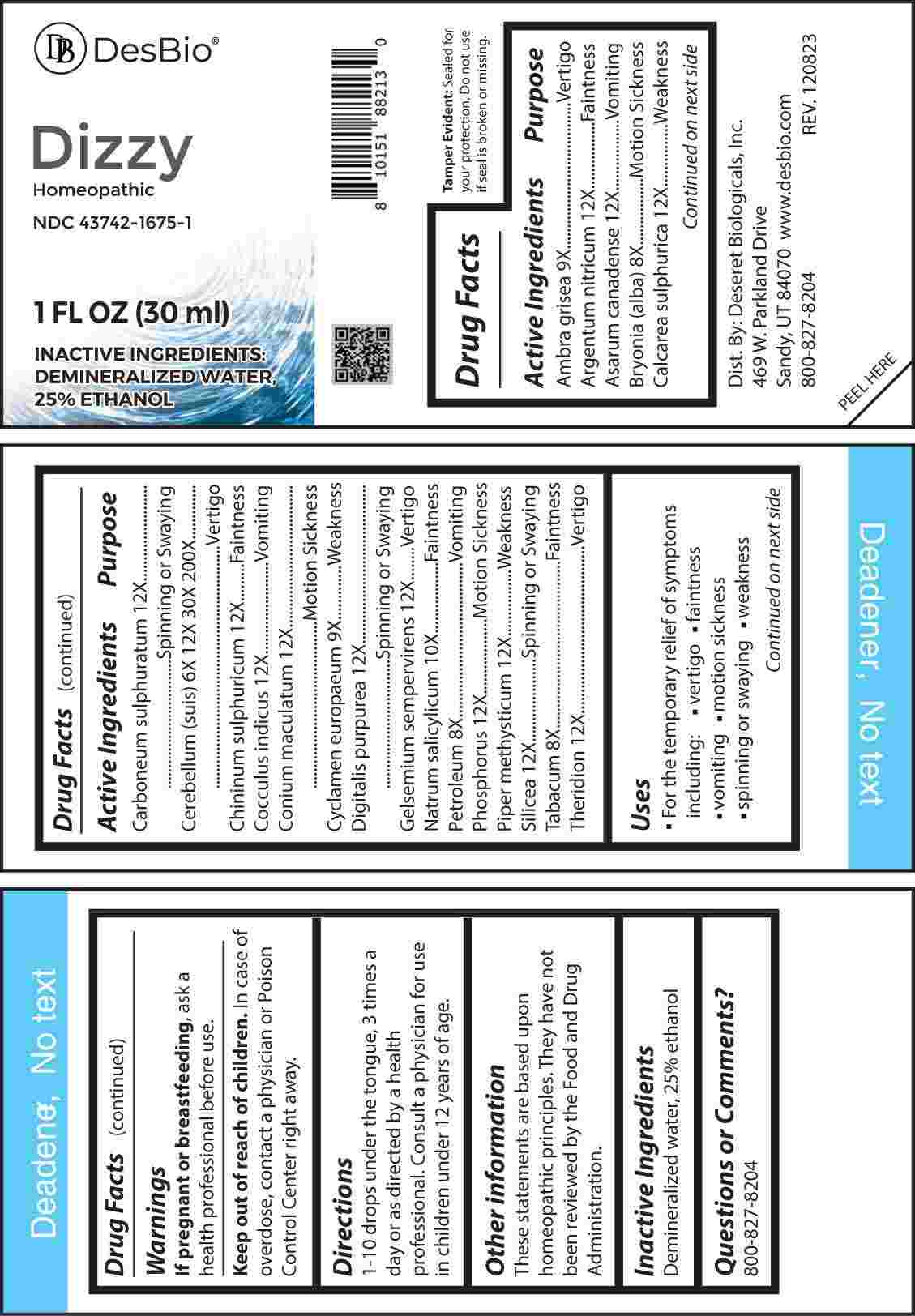 DRUG LABEL: Dizzy
NDC: 43742-1675 | Form: LIQUID
Manufacturer: Deseret Biologicals, Inc.
Category: homeopathic | Type: HUMAN OTC DRUG LABEL
Date: 20240315

ACTIVE INGREDIENTS: SUS SCROFA CEREBRUM 6 [hp_X]/1 mL; BRYONIA ALBA ROOT 8 [hp_X]/1 mL; KEROSENE 8 [hp_X]/1 mL; TOBACCO LEAF 8 [hp_X]/1 mL; AMBERGRIS 9 [hp_X]/1 mL; CYCLAMEN PURPURASCENS TUBER 9 [hp_X]/1 mL; SODIUM SALICYLATE 10 [hp_X]/1 mL; SILVER NITRATE 12 [hp_X]/1 mL; ASARUM CANADENSE ROOT 12 [hp_X]/1 mL; CALCIUM SULFATE ANHYDROUS 12 [hp_X]/1 mL; CARBON DISULFIDE 12 [hp_X]/1 mL; QUININE SULFATE 12 [hp_X]/1 mL; ANAMIRTA COCCULUS SEED 12 [hp_X]/1 mL; CONIUM MACULATUM FLOWERING TOP 12 [hp_X]/1 mL; DIGITALIS 12 [hp_X]/1 mL; GELSEMIUM SEMPERVIRENS ROOT 12 [hp_X]/1 mL; PHOSPHORUS 12 [hp_X]/1 mL; MACROPIPER METHYSTICUM ROOT 12 [hp_X]/1 mL; SILICON DIOXIDE 12 [hp_X]/1 mL; THERIDION CURASSAVICUM 12 [hp_X]/1 mL
INACTIVE INGREDIENTS: WATER; ALCOHOL

DRUG FACTS:

ACTIVE INGREDIENTS:

Ambra Grisea 9X, Argentum Nitricum 12X, Asarum Canadense 12X, Bryonia (Alba) 8X, Calcarea Sulphurica 12X, Carboneum Sulphuratum 12X, Cerebellum (Suis) 6X, 12X, 30X, 200X, Chininum Sulphuricum 12X, Cocculus Indicus 12X, Conium Maculatum 12X, Cyclamen Europaeum 9X, Digitalis Purpurea 12X, Gelsemium Sempervirens 12X, Natrum Salicylicum 10X, Petroleum 8X, Phosphorus 12X, Piper Methysticum 12X, Silicea 12X, Tabacum 8X, Theridion 12X.

PURPOSE:

Ambra Grisea - Vertigo, Argentum Nitricum - Faintness, Asarum Canadense - Vomiting, Bryonia (Alba) – Motion Sickness, Calcarea Sulphurica - Weakness, Carboneum Sulphuratum – Spinning or Swaying, Cerebellum (Suis) - Vertigo, Chininum Sulphuricum -
Faintness, Cocculus Indicus - Vomiting, Conium Maculatum – Motion Sickness, Cyclamen Europaeum - Weakness, Digitalis Purpurea – Spinning or Swaying, Gelsemium Sempervirens - Vertigo, Natrum Salicylicum - Faintness, Petroleum - Vomiting, Phosphorus – Motion Sickness, Piper Methysticum - Weakness, Silicea – Spinning or Swaying, Tabacum - Faintness, Theridion - Vertigo

USES:

• For the temporary relief of symptoms including:

• vertigo • faintness • vomiting • motion sickness

• spinning or swaying • weakness

These statements are based upon homeopathic principles. They have not been reviewed by the Food and Drug Administration.

WARNINGS:

If pregnant or breast-feeding, ask a health professional before use.

Keep out of reach of children. In case of overdose, contact a physician or Poison Control Center right away.

Tamper Evident: Sealed for your protection. Do not use if seal is broken or missing.

KEEP OUT OF REACH OF CHILDREN:

In case of overdose, contact a physician or Poison Control Center right away.

DIRECTIONS:

1-10 drops under the tongue, 3 times a day or as directed by a health professional. Consult a physician for use in children under 12 years of age.

INACTIVE INGREDIENTS:

Demineralized water, 25% ethanol

QUESTIONS:

Dist. By: Deseret Biologicals, Inc.
469 W. Parkland Drive
Sandy, UT 84070

www.desbio.co

800-827-8204

PACKAGE LABEL DISPLAY:

DesBio

Dizzy

Homeopathic

NDC 43742-1675-1

1 FL OZ (30 ml)